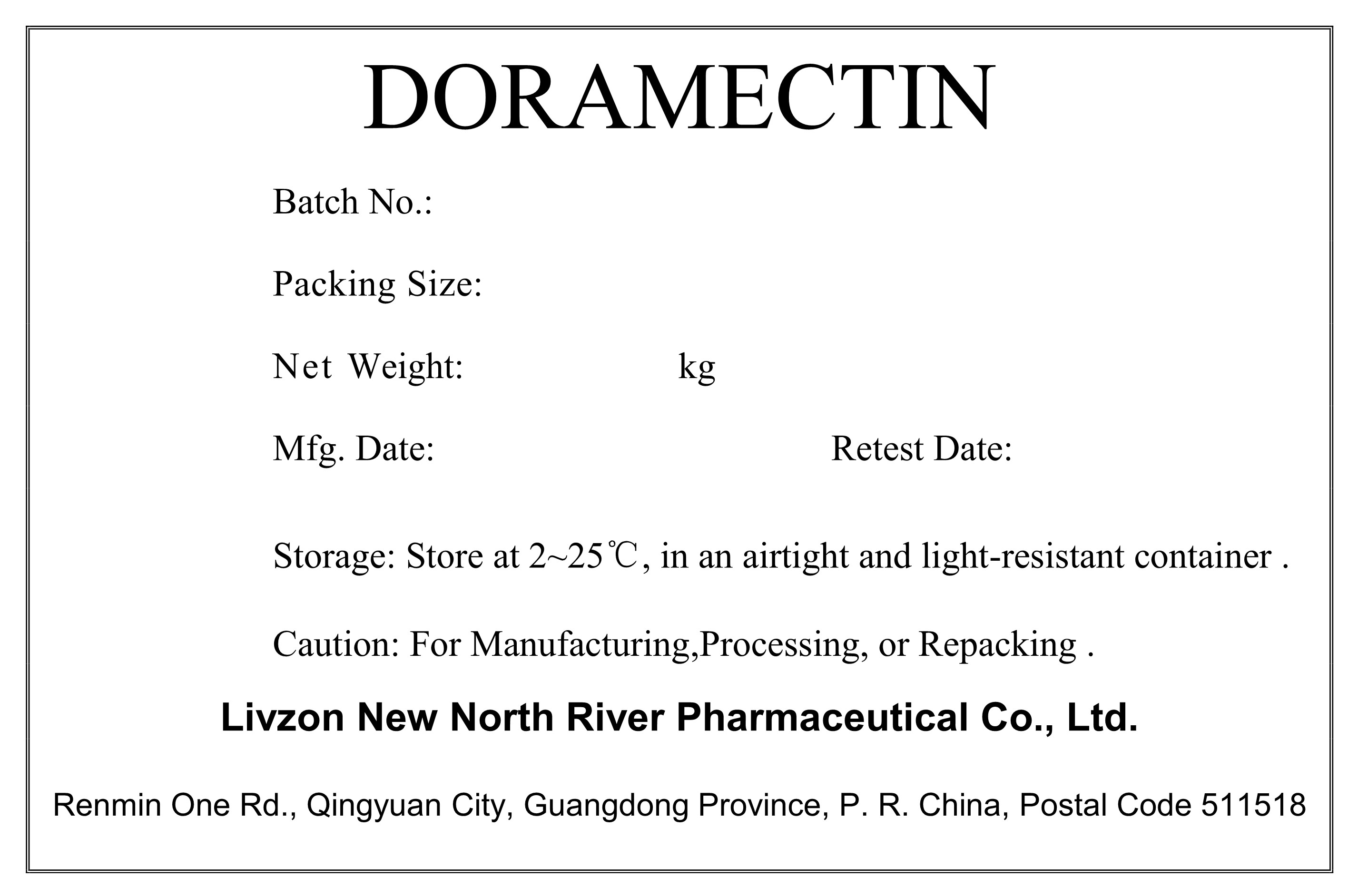 DRUG LABEL: Doramectin
NDC: 20076-2014 | Form: POWDER
Manufacturer: Livzon New North River Pharmaceutical Co., Ltd.
Category: other | Type: BULK INGREDIENT - ANIMAL DRUG
Date: 20241224

ACTIVE INGREDIENTS: DORAMECTIN 1 kg/1 kg

Doramectin